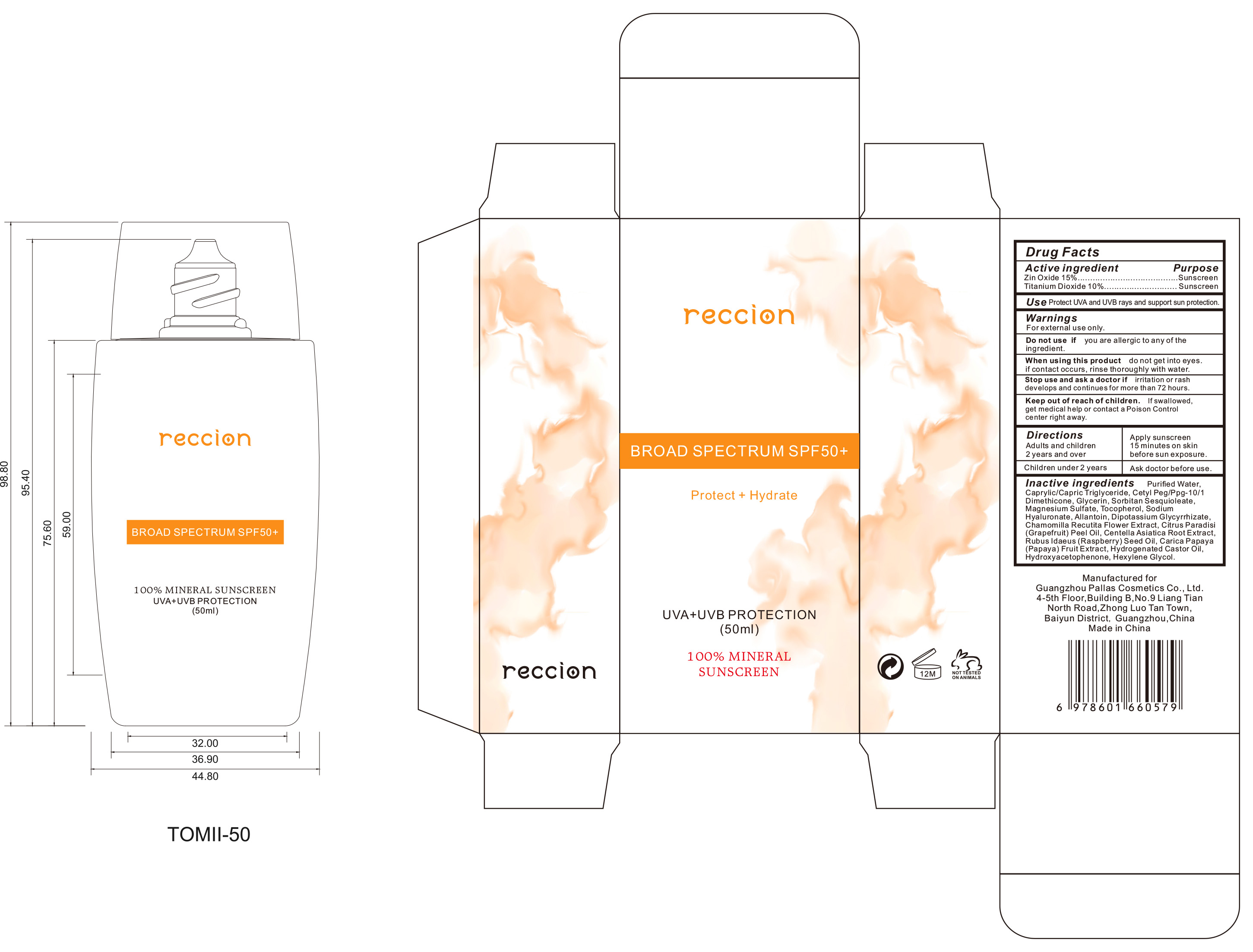 DRUG LABEL: 100% MINERAL SUNSCREEN
NDC: 84484-001 | Form: CREAM
Manufacturer: Guangzhou Pallas Cosmetics Co.,Ltd.
Category: otc | Type: HUMAN OTC DRUG LABEL
Date: 20250813

ACTIVE INGREDIENTS: ZINC OXIDE 15 g/100 mL; TITANIUM DIOXIDE 10 g/100 mL
INACTIVE INGREDIENTS: RUBUS IDAEUS (RASPBERRY) SEED OIL; HYDROGENATED CASTOR OIL; HYDROXYACETOPHENONE; HEXYLENE GLYCOL; DIPOTASSIUM GLYCYRRHIZATE; ALLANTOIN; CHAMOMILE; WATER; CAPRYLIC/CAPRIC TRIGLYCERIDE; CETYL PEG/PPG-10/1 DIMETHICONE (HLB 2); GLYCERIN; SORBITAN SESQUIOLEATE; MAGNESIUM SULFATE; TOCOPHEROL; SODIUM HYALURONATE; CITRUS PARADISI (GRAPEFRUIT) PEEL OIL; CENTELLA ASIATICA ROOT; CARICA PAPAYA (PAPAYA) FRUIT

84484-001

Active Ingredient(s)

Zin Oxide 1 5.%
Titanium Dioxide 10%

Purpose

Sunscreen

Use

Use Protect UVA and UVB rays and support sun protection.

Warnings

For external use only.

DO not use if you are allergic to any of the ingredient.

When using this product do not get into eyes. if contact occurs, rinse thoroughly with water.

Stop use and ask a doctor if irrita tion or rash develops and continues for more than 72 hours.

Keep out of reach of children. If swallowed, get medical help or contact a Poison Control
center right away.

Directions

Adults and children 2 years and over：Apply sunscreen 15 minutes on skin before sun exposure.

Children under2 years： Ask doctor before use.

Other information

No

Inactive ingredients

Purified Water, Caprylic/Capric Triglyceride, Cety| Peg/Ppg-10/1 Dimethicone, Glycerin, Sorbitan Sesquioleate，
Magnesium Sulfate, Tocopherol, Sodium Hyaluronate, Allantoin, Dipotassium Glycyrrhizate,
Chamomilla Recutita Flower E xtract, Citrus Paradisi (Grapefruit) Peel Oil, Centella Asiatica Root Extract,
Rubus ldaeus (Raspberry) Seed Oil, Carica Papaya (Papaya) Fruit Extract, Hydrogenated Castor Oil,
Hydroxyacetophenone, Hexylene Glycol.